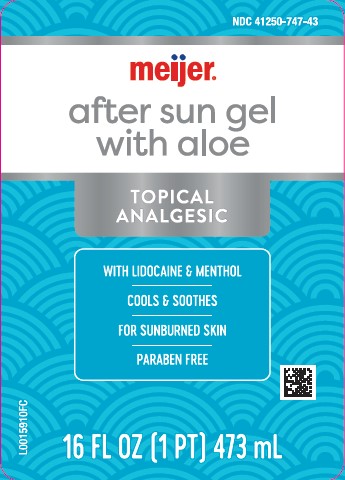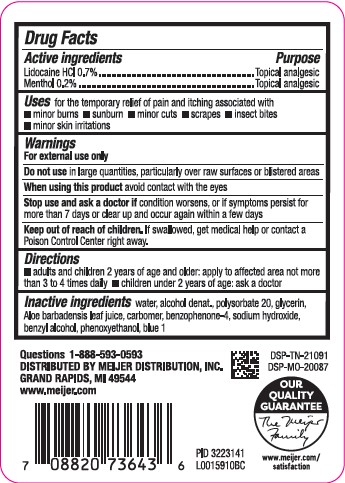 DRUG LABEL: Aloe Vera Gel
NDC: 41250-747 | Form: GEL
Manufacturer: Meijer, Inc.
Category: otc | Type: HUMAN OTC DRUG LABEL
Date: 20260219

ACTIVE INGREDIENTS: LIDOCAINE HYDROCHLORIDE 7 mg/1 mL; MENTHOL 2 mg/1 mL
INACTIVE INGREDIENTS: WATER; ALCOHOL; POLYSORBATE 20; GLYCERIN; ALOE VERA LEAF; CARBOMER HOMOPOLYMER, UNSPECIFIED TYPE; SULISOBENZONE; SODIUM HYDROXIDE; BENZYL ALCOHOL; PHENOXYETHANOL; FD&C BLUE NO. 1

Meijer 747.002/747AC
After Sun Gel with Aloe

Active ingredients

Lidocaine HCl 0.7%

Menthol 0.2%

Purpose

Topical analgesic

Uses

for the temporary relief of pain and itching associated with

- minor burns
- sunburn
- minor cuts
- scrapes
- insect bites
- minor skin irritations

Warnings

For external use only

Do not use

in large quantities, particularly over raw surfaces or blistered areas

When using this product

avoid contact with the eyes

Stop use and ask a doctor if

condition worsens, or if symptoms persist for more than 7 days or clear up and occur again within a few days

Keep out of reach of children.

If swallowed, get medical help or contact a Poison Control Center right away.

Directions

- adults and children 2 years of age and older: apply to affected area not more than 3 to 4 times daily
- children under 2 years of age: ask a doctor

inactive ingredients

water, alcohol denat., polysorbate 20, glycerin, Aloe barbadensis leaf juice, carbomer, benzophenone-4, sodium hydroxide, benzyl alcohol, phenoxyethanol, blue 1

Adverse Reaction

Questions 1-888-593-0593

DISTRIBUTED BY MEIJER DISTRIBUTION, INC.

GRAND RAPIDS, MI 49544

www.meijer.com

DSP-TN-21091

DSP-MO-20087

OUR QUALITY GUARANTEE

The Meijer Family

www.meijer.com/satisfaction

principal display panel

NDC 41250-747-43

meijer®

after sun gel

with aloe

Topical Analgesic

With Lidocaine & Menthol

Cools & Soothes

For Sunburned Skin

Paraben Free

16 FL OZ (1 PT) 473 mL